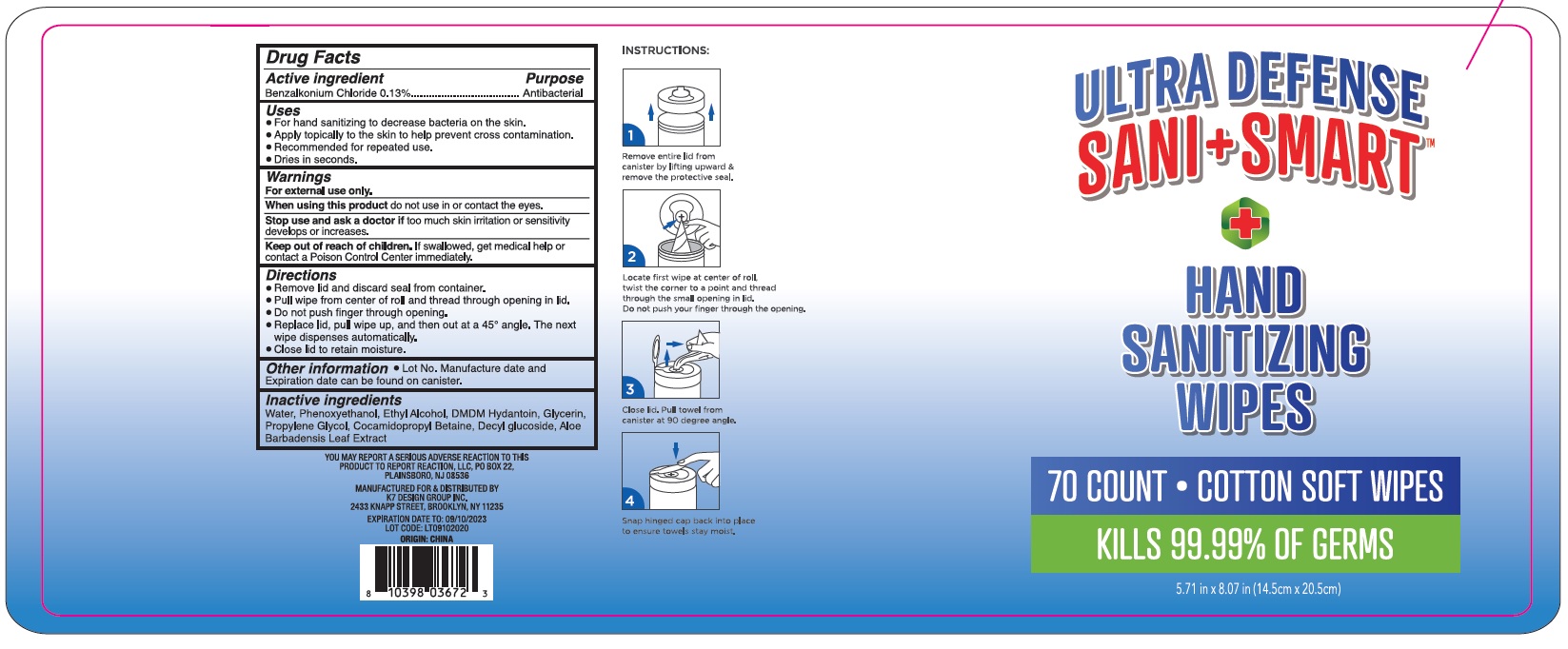 DRUG LABEL: Ultra Defense Sani Smart Hand Sanitizing Wipes
NDC: 74177-850 | Form: CLOTH
Manufacturer: K7 Design Group Inc.
Category: otc | Type: HUMAN OTC DRUG LABEL
Date: 20200826

ACTIVE INGREDIENTS: BENZALKONIUM CHLORIDE 1.3 mg/1 g
INACTIVE INGREDIENTS: COCAMIDOPROPYL BETAINE; DMDM HYDANTOIN; DECYL GLUCOSIDE; ALOE VERA LEAF; WATER; PHENOXYETHANOL; ALCOHOL; GLYCERIN; PROPYLENE GLYCOL

Ultra Defense Sani Smart Hand Sanitizing Wipes

Active ingredient

Benzalkonium Chloride 0.13%

Purpose

Antibacterial

Uses

- For hand sanitizing to decrease bactera on the skin.
- Apply topically to the skin to help prevent cross contamination.
- Recommended for repeated use.
- Dries in seconds.

Warnings

For external use only.

When using this product

do not use in or contact the eyes.

Stop use and ask a doctor if

too much skin irritation or sensitivity develops or increases.

Keep out of reach of children.

If swallowed, get medical help or contact a Poison Control Center immediately.

Directions

- Remove lid and discard seal from container.
- Pull wipe from center of roll and thread through opening in lid.
- Do not push finger through opening.
- Replace lid, pull wipe up, and then out at a 45º angle. The next wipe dispenses automatically.
- Close lid to retain moisture.

Other information

- Lot No. Manufacture date and Expiration date can be found on canister.

Inactive ingredients

Water, Phenoxyethanol, Ethyl Alcohol, DMDM Hydantoin, Glycerin, Propylene Glycol, Cocamidopropyl Betaine, Decyl glucoside, Aloe Barbadensis Leaf Extract

Company Information

YOU MAY REPORT A SERIOUS ADVERSE REACTION TO THIS PRODUCT TO REPORT REACTION, LLC, PO BOX 22, PLAINSBORO, NJ 08536

MANUFACTURED FOR & DISTRIBUTED BY K7 DESIGN GROUP INC. 2433 KNAPP STREET, BROOKLYN, NY 11235

Product Packaging - 70 COUNT

ULTRA DEFENSE

SANI+SMART

HAND

SANITIZING

WIPES

70 COUNT

COTTON SOFT WIPES

KILLS 99.99% OF GERMS

5.71 in x 8.07 in (14.5cm x 20.5cm)